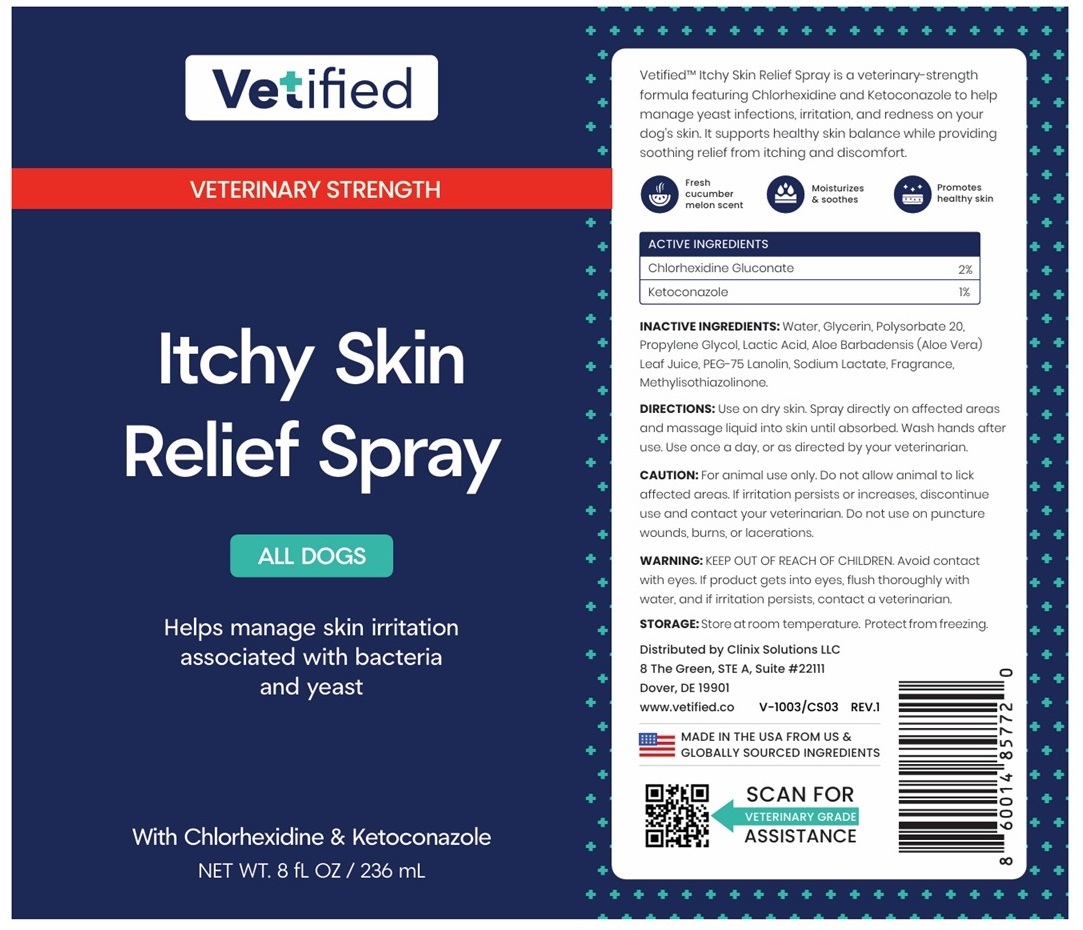 DRUG LABEL: Vetified VETERINARY STRENGTH Itchy Skin Relief ALL DOGS
NDC: 86247-003 | Form: SPRAY
Manufacturer: Clinix Solutions LLC
Category: animal | Type: OTC ANIMAL DRUG LABEL
Date: 20260112

ACTIVE INGREDIENTS: CHLORHEXIDINE GLUCONATE 20 mg/1 mL; KETOCONAZOLE 10 mg/1 mL
INACTIVE INGREDIENTS: WATER; GLYCERIN; POLYSORBATE 20; PROPYLENE GLYCOL; LACTIC ACID, UNSPECIFIED FORM; ALOE VERA LEAF JUICE; PEG-75 LANOLIN; SODIUM LACTATE; METHYLISOTHIAZOLINONE

Vetified VETERINARY STRENGTH Itchy Skin Relief Spray ALL DOGS

Vetified™ Itchy Skin Relief Spray is a veterinary-strength formula featuring Chlorhexidine and Ketoconazole to help manage yeast infections, irritation, and redness on your dog’s skin. It supports healthy skin balance while providing soothing relief from itching and discomfort.

Fresh cucumber melon scent
Moisturizes & soothes
Promotes healthy skin

ACTIVE INGREDIENTS

Chlorhexidine Gluconate 2%
Ketoconazole 1%

INACTIVE INGREDIENTS:

Water, Glycerin, Polysorbate 20, Propylene Glycol, Lactic Acid, Aloe Barbadensis (Aloe Vera) Leaf Juice, PEG-75 Lanolin, Sodium Lactate, Fragrance, Methylisothiazolinone.

DIRECTIONS:

Use on dry skin. Spray directly on affected areas and massage liquid into skin until absorbed. Wash hands after use. Use once a day, or as directed by your veterinarian.

CAUTION:

For animal use only. Do not allow animal to lick affected areas. If irritation persists or increases, discontinue use and contact your veterinarian. Do not use on puncture wounds, burns, or lacerations.

WARNING:

KEEP OUT OF REACH OF CHILDREN. Avoid contact with eyes. If product gets into eyes, flush thoroughly with water, and if irritation persists, contact a veterinarian.

STORAGE:

Store at room temperature. Protect from freezing.

Helps manage skin irritation associated with bacteria and yeast

Distributed by Clinix Solutions LLC
8 The Green, STE A, Suite #22111
Dover, DE 19901
www.vetified.co

MADE IN THE USA FROM US & GLOBALLY SOURCED INGREDIENTS